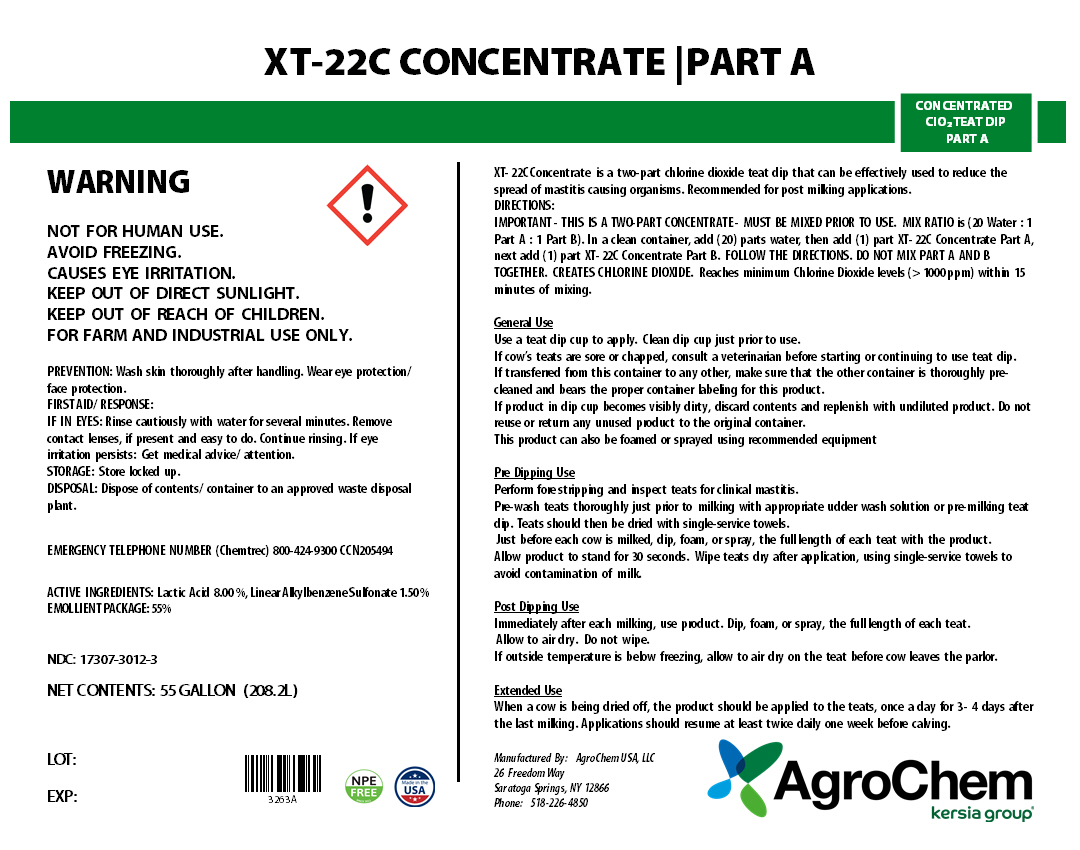 DRUG LABEL: XT 22C CONC. PART A
NDC: 17307-3012 | Form: SOLUTION
Manufacturer: AgroChem USA, LLC.
Category: animal | Type: OTC ANIMAL DRUG LABEL
Date: 20241025

ACTIVE INGREDIENTS: LACTIC ACID 0.091 kg/1 kg; DODECYLBENZENESULFONIC ACID 0.016 kg/1 kg

XT-22C CONCENTRATE PART A

XT-22C CONCENTRATE PART A

CONCENTRATED ClO2 TEAT DIP PART A

WARNING

KEEP OUT OF REACH OF CHILDREN

WARNINGS AND PRECAUTIONS

NOT FOR HUMAN USE.

AVOID FREEZING.

KEEP OUT OF DIRECT SUNLIGHT.

CAUSES SERIOUS EYE IRRITATION.

FOR FARM AND INDUSTRIAL USE ONLY.

PREVENTION: Wash skin thoroughly after handling. Wear eye protection/ face protection.

FIRST AID / RESPONSE:

IF IN EYES: Rinse cautiously with water for several minutes. Remove contact lenses, if present and easy to do. Continue rinsing. If eye irritation persists: Get medical advice/ attention.

STORAGE: Store locked up.

DISPOSAL: Dispose of contents/ container to an approved waste disposal plant

NDC: 17307-3012-3

NET CONTENTS: 55 GALLON (208.2L)

LOT:

EXP. DATE:

ACTIVE INGREDIENT: Lactic Acid 8.00 %, Linear Alkylbenzene Sulfonate 1.50 %

INACTIVE INGREDIENT

EMOLLIENT PACKAGE: 55%

XT- 22C Concentrate is a two-part chlorine dioxide teat dip that can be effectively used to reduce the spread of mastitis causing organisms. Recommended for post milking applications.

DIRECTIONS:

IMPORTANT- THIS IS A TWO-PART CONCENTRATE - MUST BE MIXED PRIOR TO USE. MIX RATIO is (20 Water: 1 Part A: 1 Part B). In a clean container, add (20) parts water, then add (1) part XT- 22C Concentrate Part A, next add (1) part XT- 22C Concentrate Part B. FOLLOW THE DIRECTIONS. DO NOT MIX PART A AND B TOGETHER. CREATES CHLORINE DIOXIDE. Reaches minimum Chlorine Dioxide levels (> 1000 ppm) within 15 minutes of mixing.

General Use

Once mixed according to directions, do not mix product with any other teat dips, or other product.

Use a teat dip cup to apply. Clean dip cup just prior to use.

If cow’s teats are sore or chapped, consult a veterinarian before starting or continuing to use teat dip.

If transferred from this container to any other, make sure that the other container is thoroughly pre-cleaned and bears the proper container labeling for this product.

If product in dip cup becomes visibly dirty, discard contents and replenish with undiluted product. Do not reuse or return any unused product to the original container.

This product can also be foamed or sprayed using recommended equipment.

Pre Dipping Use

Perform forest ripping and inspect teats for clinical mastitis.

Pre-wash teats thoroughly just prior milking with appropriate udder wash solution or pre-milking teat dip. Teats should then be dried with single-service towels.

Just before each cow is milked, dip, foam, or spray, each teat full-length into the teat dip or foam cup containing product.

Allow product to stand for 30 seconds.

Wipe teats dry after dipping, using single-service towels to avoid contamination of milk.

Post Dipping Use

Immediately after each milking, use product.

Dip each teat full-length into the teat dip cup containing product. Allow to air dry. Do not wipe.

If outside temperature is below freezing, allow to air dry on the teat before cow leaves the parlor.

Extended Use

When a cow is being dried off, the teats should be dipped in product, once a day for 3-4 days after the last milking.

Dipping should be resumed at least twice daily one week before calving.

Manufactured By:

AgroChem USA, LLC 26 Freedom Way • Saratoga Springs, NY 12866 • (518)226-4850